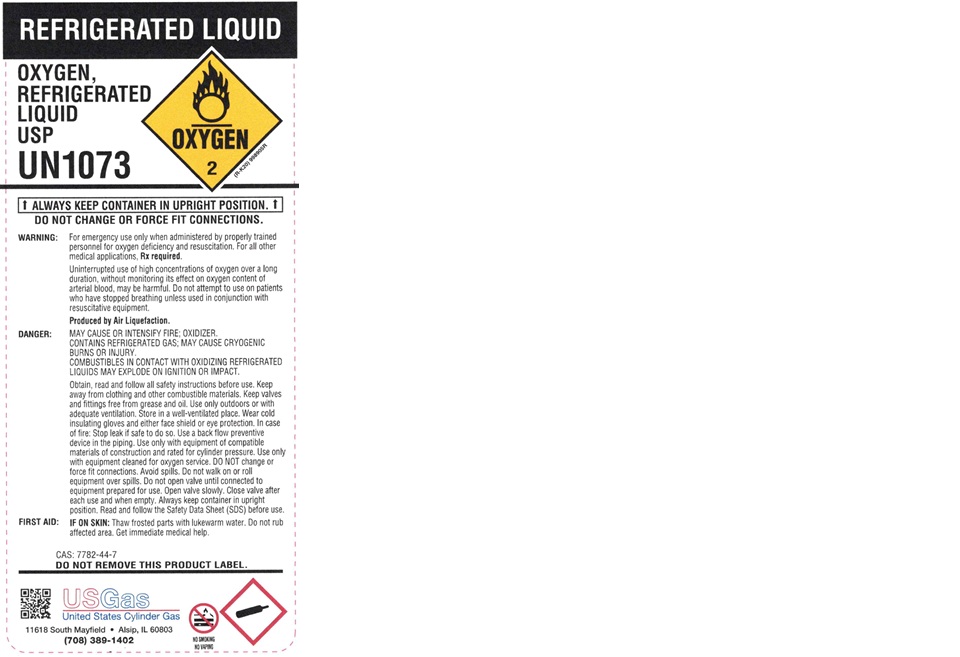 DRUG LABEL: Reconstituted Air
NDC: 68877-009 | Form: GAS
Manufacturer: United States Cylinder Gas Corporation
Category: prescription | Type: HUMAN PRESCRIPTION DRUG LABEL
Date: 20251009

ACTIVE INGREDIENTS: OXYGEN 210 mL/1 L
INACTIVE INGREDIENTS: NITROGEN 790 mL/1 L

Reconstituted Air

PACKAGE LABEL

AIR, COMPRESSED

UN1002

Medical Air, USP MIXTURE OF OXYGEN USP AND NITROGEN NF

WARNING: For breathing support when use by properly trained personnel. For medical applications, RX only. Administered of Medical Air may be hazardous or contraindicated. For use only by or under the supervision of a licensed practitioner who is experienced in the use and administration of Medical Air and is familiar with the indications, effects, dosages, methods, and frequency, and duration of administration, and with the hazards, contraindications and side effects, and the precautions to be taken. WARNING: CONTAINS GAS UNDER PRESSURE; MAY EXPLODE IF HEATED. SUPPORTS COMBUSTING. Do not handle until all safety precautions have been read and understood. Protect from sunlight when ambient temperature exceeds 52 C (125 F). Use a back flow preventive device in the piping. Close valve after each use and when empty. Use only with equipment rated for cylinder pressure. Do not open valve until connected to equipment prepared for use. Read and follow the Safety Data Sheet (SDS) before use.

CAS: 132259-10-0 DO NOT REMOVE THIS PRODUCT LABEL.

US GAS

United States Cylinder Gas

11618 South Mayfield Alsip, IL 60803 (708) 389-1402